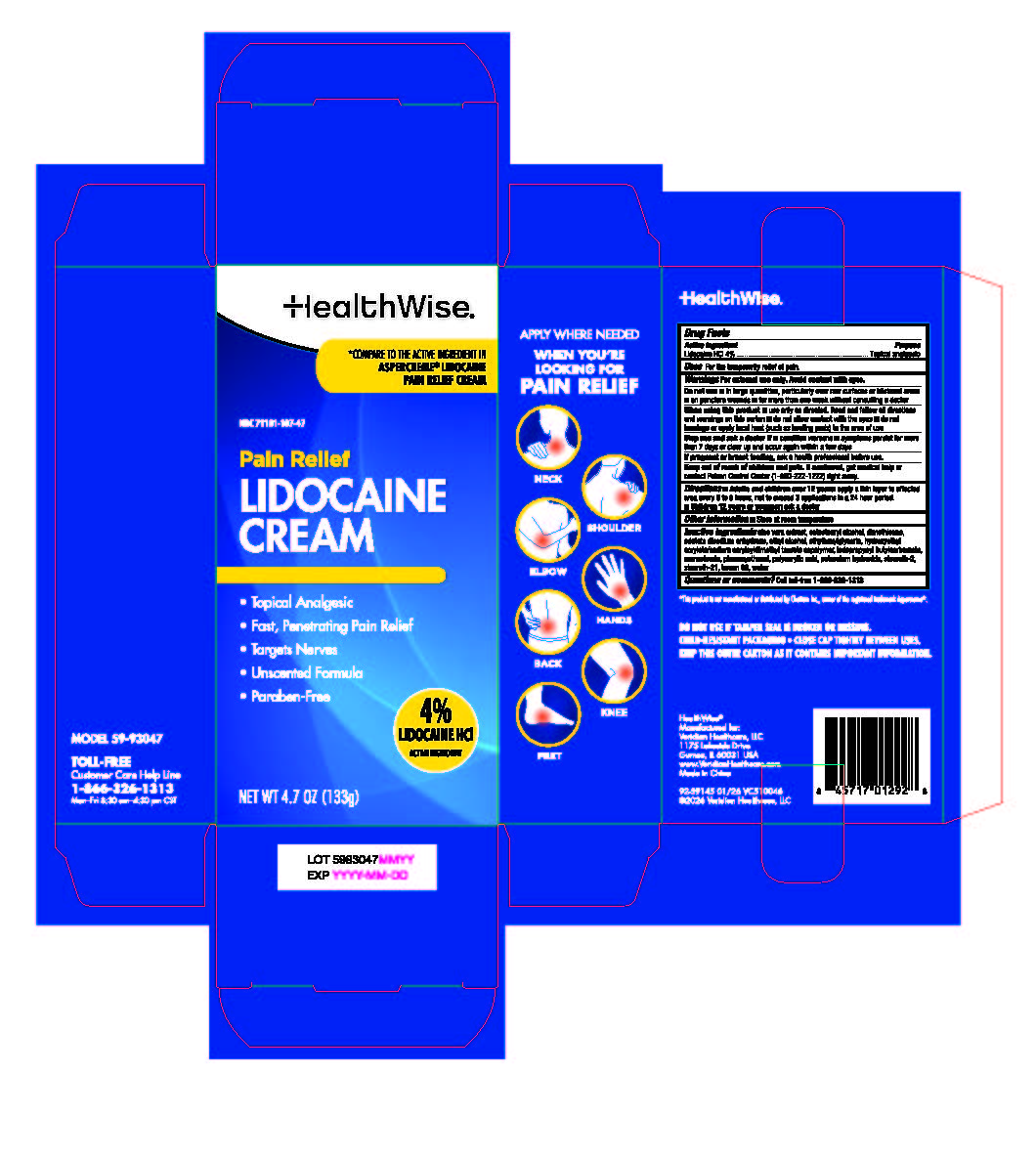 DRUG LABEL: HealthWise Pain Relief Lidocaine
NDC: 71101-107 | Form: CREAM
Manufacturer: Veridian Healthcare	
Category: otc | Type: HUMAN OTC DRUG LABEL
Date: 20260228

ACTIVE INGREDIENTS: LIDOCAINE HYDROCHLORIDE 4 g/100 g
INACTIVE INGREDIENTS: WATER; ALCOHOL; POLYACRYLIC ACID (250000 MW); HYDROXYETHYL ACRYLATE/SODIUM ACRYLOYLDIMETHYL TAURATE COPOLYMER (45000 MPA.S AT 1%); DIMETHICONE; EDETATE DISODIUM ANHYDROUS; GLYCERYL 1-STEARATE; STEARETH-2; ALOE VERA LEAF; POLYSORBATE 60; PHENOXYETHANOL; STEARETH-21; CETOSTEARYL ALCOHOL; POTASSIUM HYDROXIDE; ETHYLHEXYLGLYCERIN; IODOPROPYNYL BUTYLCARBAMATE

HealthWise Pain Relief Lidocaine Cream

Active ingredient

Lidocaine HCl 4%

Purpose

Topical analgesic

Use

For the temporarily relief of pain

Warnings

For external use only. Avoid contact with eyes.

Do not use

- in large quantities, particularly over raw surfaces or blistered areas
- on puncture wounds
- for more than one week without consulting a doctor

When using this product

- use only as directed. Read and follow all directions and warnings on this carton.
- do not allow contact with the eyes
- do not bandage or apply local heat (such as heating pads) to the area of use

Stop use and ask a doctor if

- condition worsens
- symptoms persist for more than 7 days or clear up and occur again within a few days

If pregnant or breast-feeding,

ask a health professional before use.

Keep out of reach of children.

If swallowed, get medical help or contact a Poison Control Center (800-222-1222) right away.

Directions

adults and children over 12 years:

- apply a thin layer to affected area every 6 to 8 hours, not to exceed 3 applications in a 24 hour period

children 12 years or younger: ask a doctor

Inactive ingredients

aloe vera extract, cetostearyl alcohol, dimethicone, edetate disodium anhydrous, ethyl alcohol, ethylhexylglycerin, hydroxyethyl acrylate/sodium acryloyldimethyl taurate copolymer, iodopropynyl butylcarbamate, monostearin, phenoxyethanol, polyacrylic acid, potassium hydroxide, steareth-2, steareth-21, tween 60, water